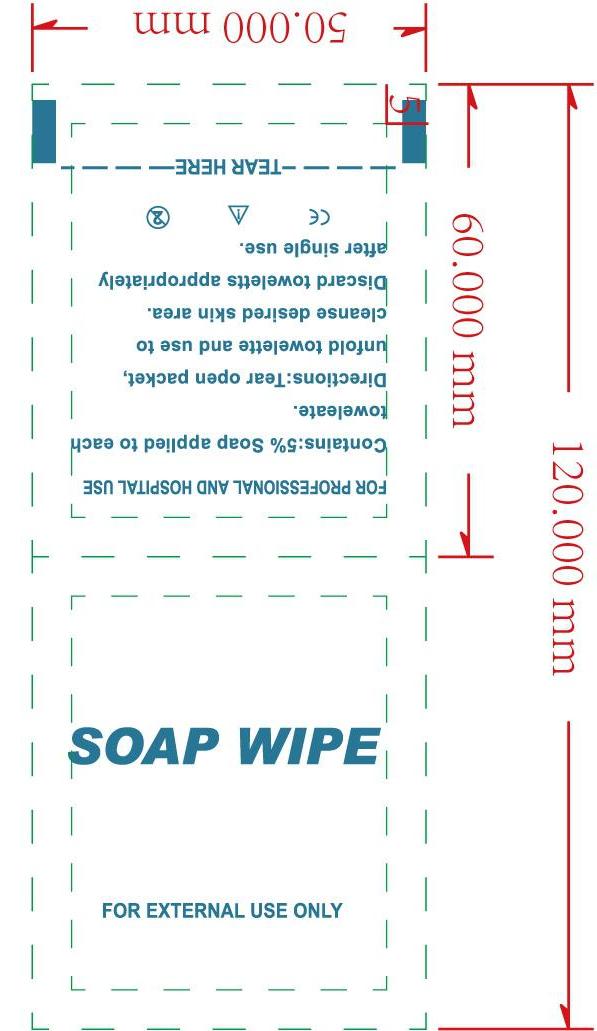 DRUG LABEL: Skin Cleaning Care Wipes
NDC: 84449-005 | Form: PATCH
Manufacturer: SHENZHEN BENLIJU BIO-TECH CO.,LTD
Category: otc | Type: HUMAN OTC DRUG LABEL
Date: 20260105

ACTIVE INGREDIENTS: ETHYLHEXYLGLYCERIN 10 mg/1 g; SALICYLIC ACID 10 mg/1 g; ALLANTOIN 10 mg/1 g; ALOE 10 mg/1 g; HAMAMELIS VIRGINIANA TOP 10 mg/1 g; GLYCERIN 10 mg/1 g
INACTIVE INGREDIENTS: WATER; PHENOXYETHANOL

ACTIVE INGREDIENT

AloeVera,Glycerin,salicylate,Hamamelis Extract,Ethylhexylglycerin,allantoin

PURPOSE

disinfect

INDICATIONS AND USAGE

For Daily cleansing and care of human skin or removal of make-up and nails for beauty and cosmetic purposes.

WARNINGS

*For extemal use only.
*Flammable. keep away from fire or flame.

Do not use " with electrocautery procedures " in the eyes. lf contact occurs, flush eyes with water.

When using this product keep out of eyes, ears, and mouth. In case of contact with eyes, rinse eyes thoroughly with water.

*Stop use if irritation and redness develop. If condition persists consult your health care practioner.

*Stop use and ask a doctor if irritation or rash occurs. These may be signs of a serious condition.

Keep out of reach of children. If swallowed, get medical help or contact a Poison Control Center right away.

DOSAGE AND ADMINISTRATION

For Daily cleansing and care of human skin or removal of make-up and nails for beauty and cosmetic purposes..One piece at a time.

STORAGE AND HANDLING

Store at room temperature.

INACTIVE INGREDIENT

water, phenoxyethanol